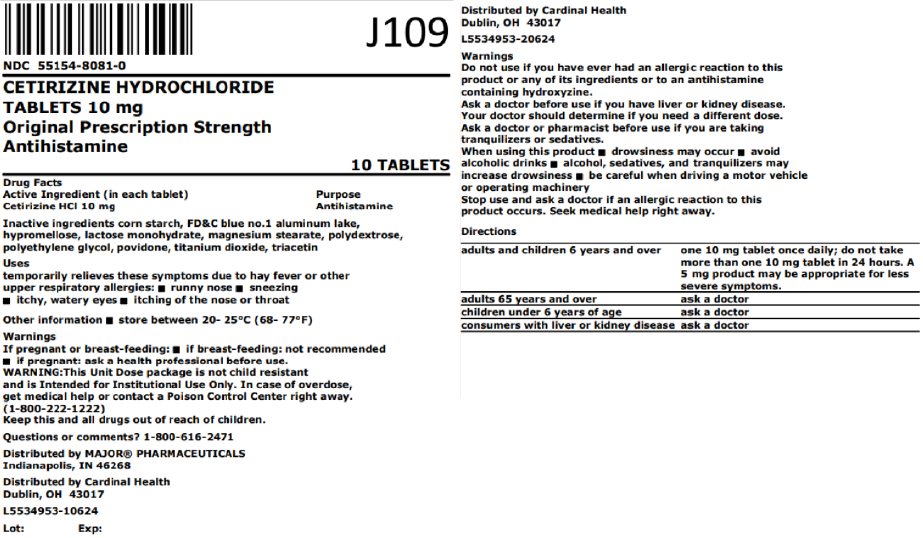 DRUG LABEL: Cetirizine
NDC: 55154-8081 | Form: TABLET, FILM COATED
Manufacturer: Cardinal Health 107, LLC
Category: otc | Type: HUMAN OTC DRUG LABEL
Date: 20260216

ACTIVE INGREDIENTS: CETIRIZINE HYDROCHLORIDE 10 mg/1 1
INACTIVE INGREDIENTS: STARCH, CORN; FD&C BLUE NO. 1 ALUMINUM LAKE; HYPROMELLOSE, UNSPECIFIED; LACTOSE MONOHYDRATE; MAGNESIUM STEARATE; POLYDEXTROSE; POLYETHYLENE GLYCOL, UNSPECIFIED; POVIDONE, UNSPECIFIED; TITANIUM DIOXIDE; TRIACETIN

Cetirizine Drug Facts

Active ingredient (in each tablet)

Cetirizine HCl 10 mg

Purpose

Antihistamine

Uses

temporarily relieves these symptoms due to hay fever or other upper respiratory allergies:

- runny nose
- sneezing
- itchy, watery eyes
- itching of the nose or throat

Warnings

Do not use

if you have ever had an allergic reaction to this product or any of its ingredients or to an antihistamine containing hydroxyzine.

Ask a doctor before use if you have

liver or kidney disease. Your doctor should determine if you need a different dose.

Ask a doctor or pharmacist before use if you are

taking tranquilizers or sedatives.

When using this product

- drowsiness may occur
- avoid alcoholic drinks
- alcohol, sedatives, and tranquilizers may increase drowsiness
- be careful when driving a motor vehicle or operating machinery

Stop use and ask a doctor if

an allergic reaction to this product occurs. Seek medical help right away.

If pregnant or breast-feeding:

- if breast-feeding: not recommended
- if pregnant: ask a health professional before use.

Keep out of reach of children.

In case of overdose, get medical help or contact a Poison Control Center right away. (1-800-222-1222)

Directions

adults and children 6 years and over | one 10 mg tablet once daily; do not take more than one 10 mg tablet in 24 hours. A 5 mg product may be appropriate for less severe symptoms.
adults 65 years and over | ask a doctor
children under 6 years of age | ask a doctor
consumers with liver or kidney disease | ask a doctor

Other information

- store between 20-25°C (68-77°F)
- do not use if printed foil under cap is broken or missing

Inactive ingredients

corn starch, FD&C blue no. 1 aluminum lake, hypromellose, lactose monohydrate, magnesium stearate, polydextrose, polyethylene glycol, povidone, titanium dioxide, triacetin

Questions or comments?

1-800-719-9260

.

*This product is not manufactured or distributed by Johnson & Johnson Consumer Inc., McNeil Consumer Healthcare Division, distributor of Zyrtec®

Gluten Free

Distributed by:

MAJOR® PHARMACEUTICALS

Indianapolis, IN 46268

(800) 616-2471

www.majorpharmaceuticals.com

Overbagged with 10 film-coated tablets per bag, NDC 55154-8081-0

WARNING: This Unit Dose package is not child resistant and is Intended for Institutional Use Only. Keep this and all drugs out of the reach of children.

Distributed By:

Cardinal Health

Dublin, OH 43017

L5534953-10624 / L5534953-20624

Rev. 07/24 | M-05 | Re-Order No. 700683

Principal Display Panel

NDC 55154-8081-0

CETIRIZINE HYDROCHLORIDE

TABLETS 10 mg

Original Prescription Strength

Antihistamine

10 TABLETS